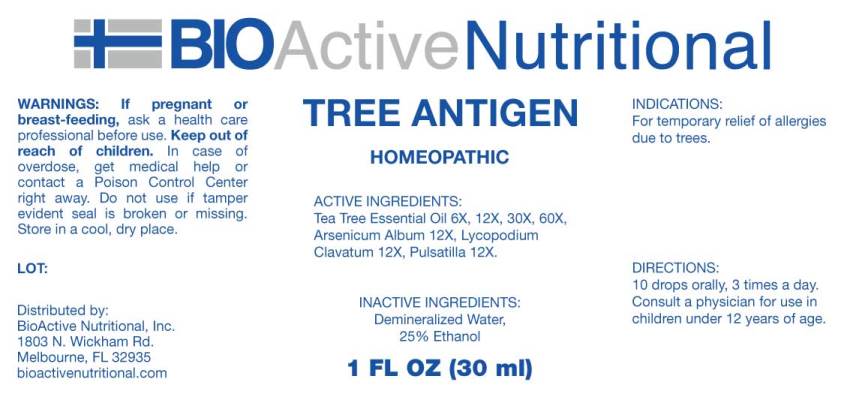 DRUG LABEL: Tree Antigen
NDC: 43857-0520 | Form: LIQUID
Manufacturer: BioActive Nutritional, Inc.
Category: homeopathic | Type: HUMAN OTC DRUG LABEL
Date: 20230607

ACTIVE INGREDIENTS: TEA TREE OIL 6 [hp_X]/1 mL; ARSENIC TRIOXIDE 12 [hp_X]/1 mL; LYCOPODIUM CLAVATUM SPORE 12 [hp_X]/1 mL; PULSATILLA PRATENSIS WHOLE 12 [hp_X]/1 mL
INACTIVE INGREDIENTS: WATER; ALCOHOL

Drug Facts:

ACTIVE INGREDIENTS:

Tea Tree Essential Oil 6X, 12X, 30X, 60X, Arsenicum Album 12X, Lycopodium Clavatum 12X, Pulsatilla (Pratensis) 12X.

INDICATIONS:

For temporary relief of allergies due to trees.

WARNINGS:

If pregnant or breast-feeding, ask a health care professional before use.

Keep out of reach of children. In case of overdose, get medical help or contact a Poison Control Center right away.

Do not use if tamper evident seal is broken or missing.

Store in a cool, dry place.

Keep out of reach of children. In case of overdose, get medical help or contact a Poison Control Center right away.

DIRECTIONS:

10 drops orally, 3 times a day. Consult a physician for use in children under 12 years of age.

INDICATIONS:

For temporary relief of allergies due to trees.

INACTIVE INGREDIENTS:

Demineralized Water, 25% Ethanol

QUESTIONS:

Distributed by:

BioActive Nutritional, Inc.

1803 N. Wickham Rd.

Melbourne, FL 32935

bioactivenutritional.com

PACKAGE LABEL DISPLAY:

BIOActive Nutritional

TREE ANTIGEN

HOMEOPATHIC

1 FL OZ (30 ml)